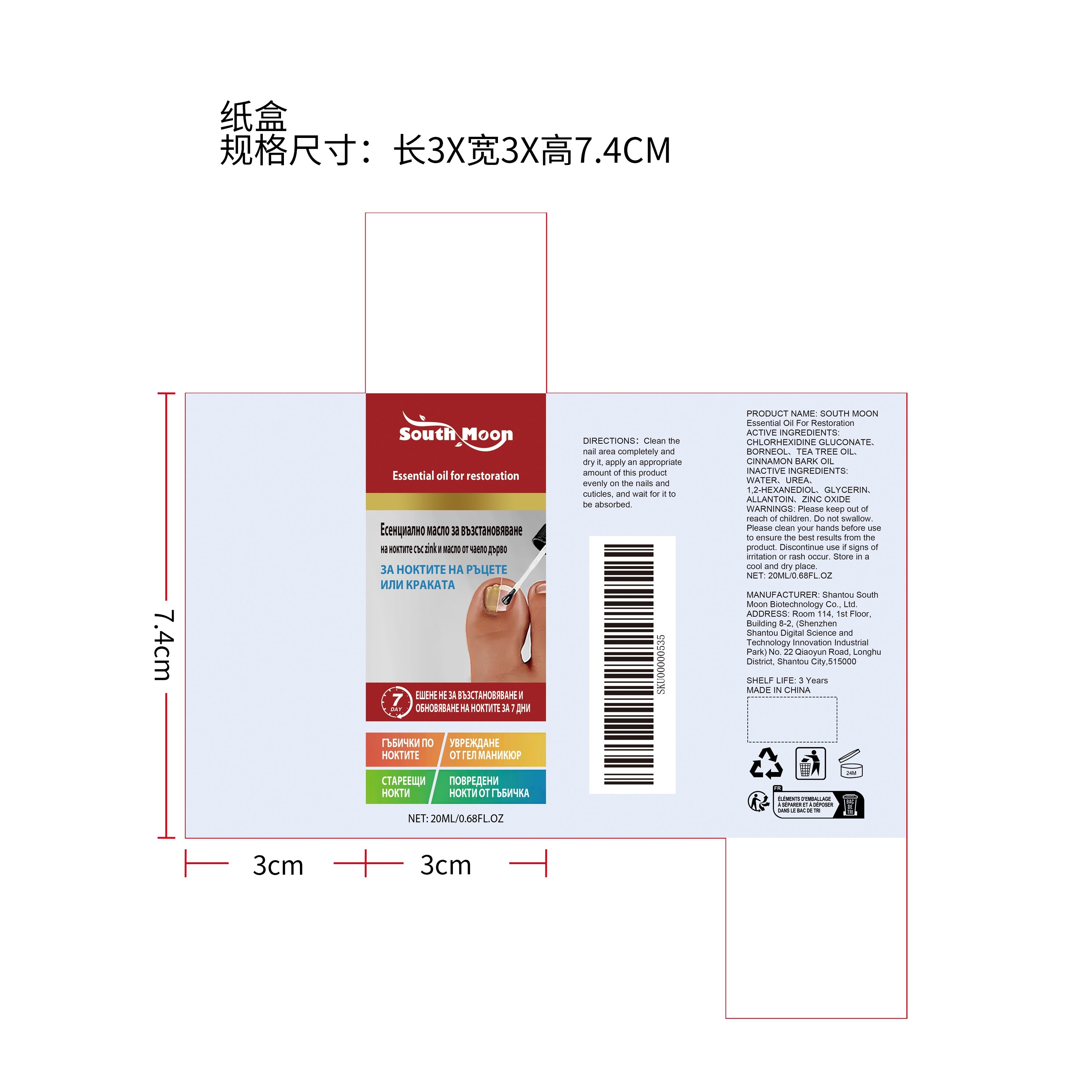 DRUG LABEL: SOUTH MOON Essential Oil For Restoration
NDC: 84983-020 | Form: LIQUID
Manufacturer: Shantou South Moon Biotechnology Co., Ltd.
Category: otc | Type: HUMAN OTC DRUG LABEL
Date: 20260126

ACTIVE INGREDIENTS: TEA TREE OIL 0.004 mg/20 mg; BORNEOL 0.004 mg/20 mg; CINNAMON BARK OIL 0.004 mg/20 mg
INACTIVE INGREDIENTS: WATER 18.84 mg/20 mg; UREA 1 mg/20 mg; CHLORHEXIDINE GLUCONATE 0.004 mg/20 mg; GLYCERIN 0.02 mg/20 mg; ZINC OXIDE 0.004 mg/20 mg; ALLANTOIN 0.02 mg/20 mg; 1,2-HEXANEDIOL 0.1 mg/20 mg

ACTIVE INGREDIENT

CHLORHEXIDINE GLUCONATE、BORNEOL、TEA TREE OIL、CINNAMON BARK OIL

PURPOSE

1. Powerful antibacterial: effectively sterilizes, inhibits fungal growth, and quickly relieves onychomycosis.

2. Deep repair: Go deep into the root of the nail to promote healthy nail growth and repair damaged tissue.

3. Mild ingredients: It uses mild ingredients, does not contain harmful chemicals, is safe, mild and non-irritating.

4. Easy to use: easy to apply, quickly absorbed, and leaves no greasy feeling.

5. Provide long-term protection to prevent the recurrence of onychomycosis and keep nails healthy.

6. Mild formula, suitable for long-term use without side effects.

7. Provides anti-inflammatory effects, reduces redness, swelling and pain, and relieves discomfort.

8. Suitable for all nail types, comprehensive care for nail health.

9. Provides moisturizing effect and prevents nails from dryness and brittleness.

10. Can stimulate blood circulation and promote nail growth.

11. Contains nourishing ingredients to enhance nail toughness and prevent breakage.

12. No irritating smell, more comfortable to use.

13. Quick results, significantly improving onychomycosis in a short period of time.

14. Provide a protective layer to resist external pollution and bacterial invasion.

15. Suitable for use by the whole family, including the elderly and adults.

WHEN USING

Penetrates deeply into the base of nails to fight nail fungus; repairs damaged nail beds and promotes nail growth; penetrates deeply to restore nail luster.

WARNINGS

Please keep out of reach of children. Do not swallow.Please clean your hands before use to ensure the best results from the product. Discontinue use if signs of irritation or rash occur. Store in a cool and dry place.

DO NOT USE

Discontinue use if signs of irritation or rash occur.

STOP USE

Discontinue use if signs of irritation or rash occur.

KEEP OUT OF REACH OF CHILDREN

Please keep out of reach of children. Do not swallow.

STORAGE AND HANDLING

Store in a cool and dry place.

INACTIVE INGREDIENT

WATER、UREA、1,2-HEXANEDIOL、GLYCERIN、ALLANTOIN、ZINC OXIDE

INDICATIONS AND USAGE

Penetrates deeply into the base of nails to fight nail fungus; repairs damaged nail beds and promotes nail growth; penetrates deeply to restore nail luster.

DOSAGE AND ADMINISTRATION

Penetrates deeply into the base of nails to fight nail fungus; repairs damaged nail beds and promotes nail growth; penetrates deeply to restore nail luster.